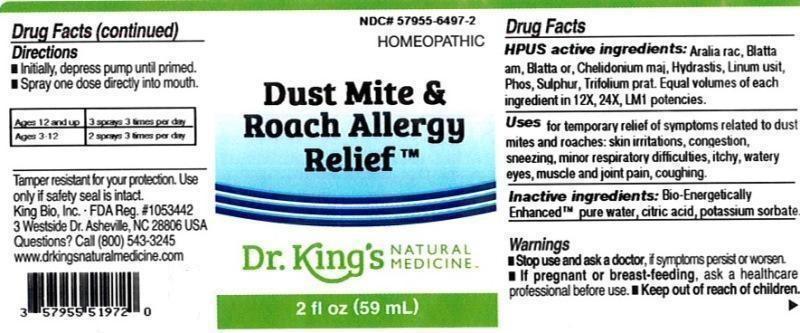 DRUG LABEL: Dust Mite and Roach Allergy Relief
NDC: 57955-6497 | Form: LIQUID
Manufacturer: King Bio Inc.
Category: homeopathic | Type: HUMAN OTC DRUG LABEL
Date: 20160713

ACTIVE INGREDIENTS: ARALIA RACEMOSA ROOT 12 [hp_X]/59 mL; PERIPLANETA AMERICANA 12 [hp_X]/59 mL; BLATTA ORIENTALIS 12 [hp_X]/59 mL; CHELIDONIUM MAJUS 12 [hp_X]/59 mL; GOLDENSEAL 12 [hp_X]/59 mL; FLAX SEED 12 [hp_X]/59 mL; PHOSPHORUS 12 [hp_X]/59 mL; SULFUR 12 [hp_X]/59 mL; TRIFOLIUM PRATENSE FLOWER 12 [hp_X]/59 mL
INACTIVE INGREDIENTS: ANHYDROUS CITRIC ACID; POTASSIUM SORBATE; WATER

Dust Mite and Roach Allergy Relief

ACTIVE INGREDIENT

Drug Facts__________________________________________________________________________________________________________

HPUS active ingredients: Aralia racemosa, Blatta americana, Blatta orientalis, Chelidonium majus, Hydrastis canadensis, Linum usitatissimum, Phosphorus, Sulphur, Trifolium pratense. Equal volumes of each ingredient in 12X, 24X, LM1 potencies.

INDICATIONS AND USAGE

Uses for temporary relief of symptoms related to dust mites and roaches: skin irritations, congestion, sneezing, minor respiratory difficulties, itchy, watery eyes, muscle and joint pain, coughing.

Inactive Ingredients:

Bio-Energetically Enhanced™ pure water, citric acid and potassium sorbate.

Warnings

- Stop use and ask your doctor if symptoms persist or worsen.
- If pregnant or breast-feeding, ask a healthcare professional before use.

- Keep out of reach of children.

Directions

- Initially, depress pump until primed.
- Spray one dose directly into mouth.
- Ages 12 and up: 3 sprays 3 times per day.
- Ages 3-12: 2 sprays 3 times per day.

OTHER SAFETY INFORMATION

Tamper resistant for your protection. Use only if seal is intact.

PURPOSE

Uses for temporary relief of symptoms related to dust mites and roaches:

- skin irritations
- congestion
- sneezing
- minor respiratory difficulties
- itchy, watery eyes
- muscle and joint pain
- coughing